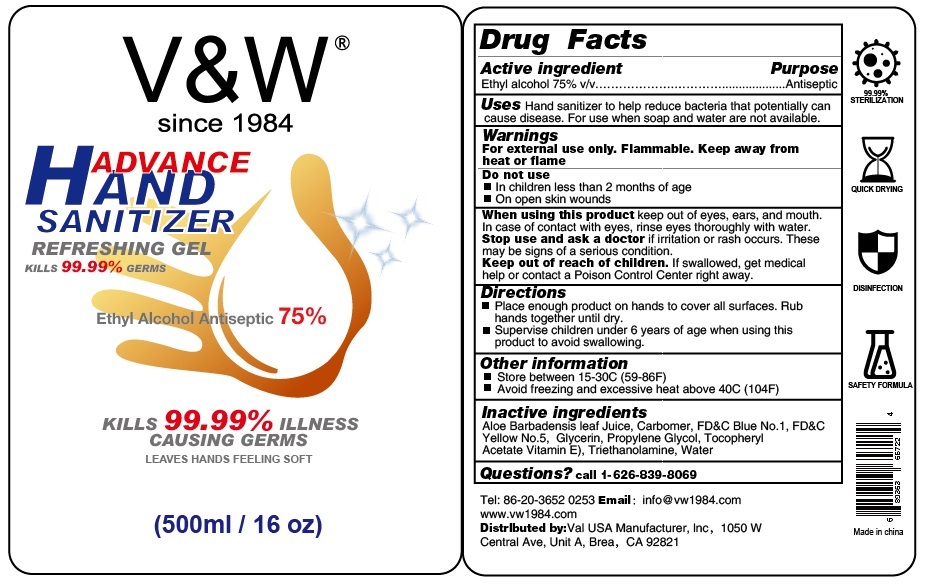 DRUG LABEL: V W
NDC: 76687-008 | Form: GEL
Manufacturer: VAL USA Manufacturer Inc
Category: otc | Type: HUMAN OTC DRUG LABEL
Date: 20210812

ACTIVE INGREDIENTS: ALCOHOL 75 mL/100 mL
INACTIVE INGREDIENTS: PROPYLENE GLYCOL; TROLAMINE; FD&C BLUE NO. 1; FD&C YELLOW NO. 5; GLYCERIN; ALOE VERA LEAF; WATER; CARBOMER HOMOPOLYMER, UNSPECIFIED TYPE; .ALPHA.-TOCOPHEROL ACETATE

VAL-GEL

Active Ingredient(s)

Alcohol 75% v/v. Purpose: Antiseptic

Purpose

Antiseptic, Hand Sanitizer

Use

Hand Sanitizer to help reduce bacteria that potentially can cause disease. For use when soap and water are not available.

Warnings

For external use only. Flammable. Keep away from heat or flame

Do not use

- in children less than 2 months of age
- on open skin wounds

When using this product keep out of eyes, ears, and mouth. In case of contact with eyes, rinse eyes thoroughly with water.
Stop use and ask a doctor if irritation or rash occurs. These may be signs of a serious condition.
Keep out of reach of children. If swallowed, get medical help or contact a Poison Control Center right away.

Stop use and ask a doctor if irritation or rash occurs. These may be signs of a serious condition.

Keep out of reach of children. If swallowed, get medical help or contact a Poison Control Center right away.

Directions

- Place enough product on hands to cover all surfaces. Rub hands together until dry.
- Supervise children under 6 years of age when using this product to avoid swallowing.

Other information

- Store between 15-30C (59-86F)
- Avoid freezing and excessive heat above 40C (104F)

Inactive ingredients

Aloe Barbadensis leaf Juice, Carbomer, FD&C Blue No.1, FD&C Yellow No.5, Glycerin, Propylene Glycol, Tocopheryl Acetate Vitamin E), Triethanolamine, Water

Package Label - Principal Display Panel

500 mL NDC: 76687-005-13